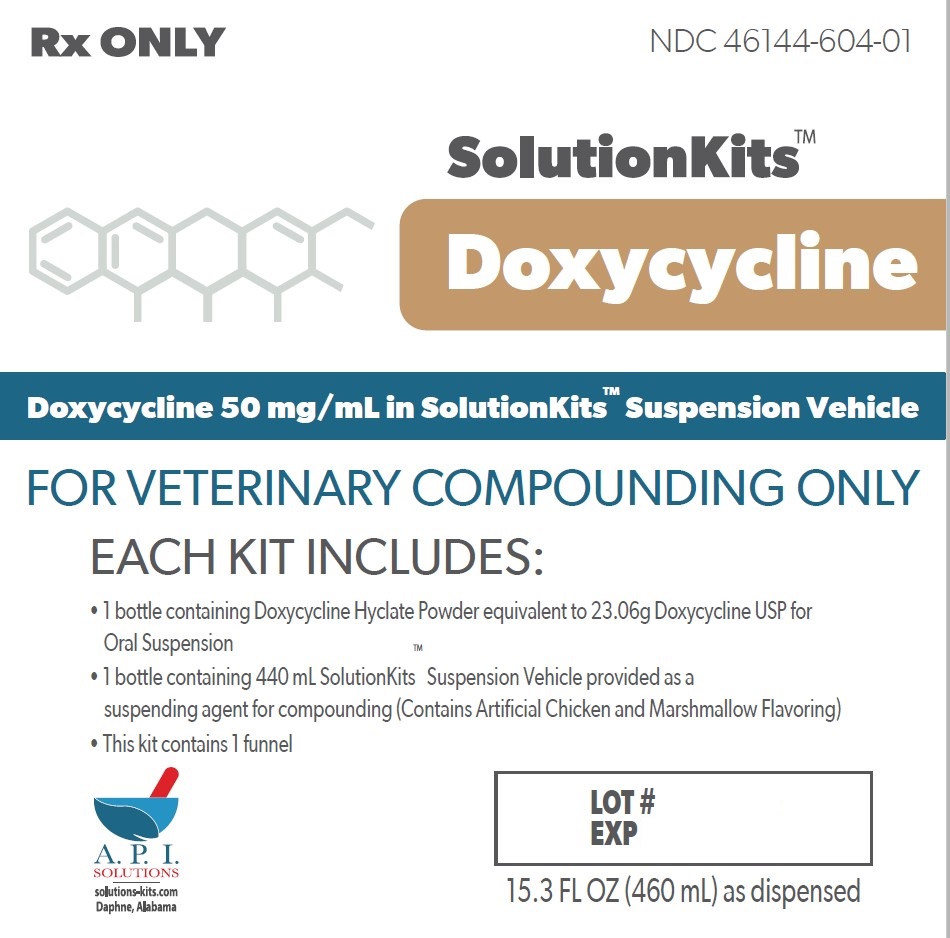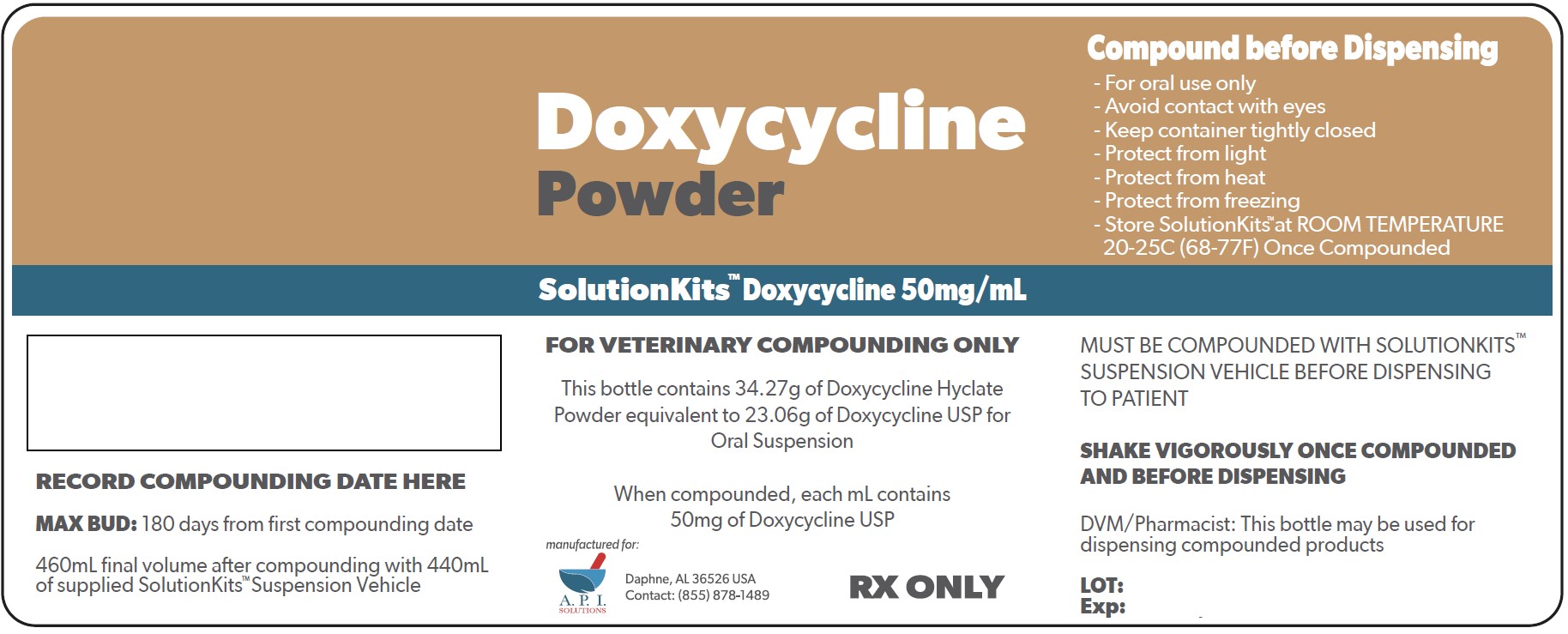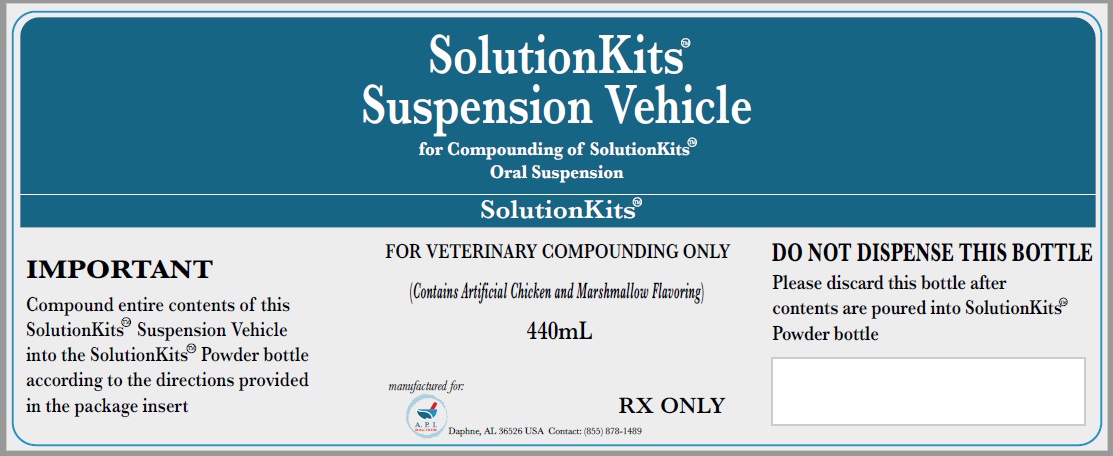 DRUG LABEL: SolutitionKits
NDC: 46144-604 | Form: KIT | Route: NOT APPLICABLE
Manufacturer: API Solutions
Category: other | Type: BULK INGREDIENT - ANIMAL DRUG
Date: 20250323

ACTIVE INGREDIENTS: DOXYCYCLINE HYCLATE 1 g/1 g
INACTIVE INGREDIENTS: MEDIUM-CHAIN TRIGLYCERIDES; COCONUT OIL; BUTYLATED HYDROXYANISOLE; POLYGLYCERYL-3 OLEATE; SILICON DIOXIDE; .ALPHA.-TOCOPHEROL

SolutionsKits Doxycycline Hyclate USP

SolutionKits™Doxycycline

Doxycycline 50 mg/mL in SolutionKits™ Suspension Vehicle

FOR VETERINARY COMPOUNDING ONLY

Each kit includes:

1 bottle containing Doxycycline Hyclate Powder equivalent to 23.06g Doxycycline USP for Oral Suspension

1 bottle containing 440 mL SolutionKits™ Suspension Vehicle provided as a suspending agent for compounding (Contains Artificial Chicken and Marshmallow Flavoring)

This kit contains 1 funnel

A.P.I.

Solutions

Daphne, AL USA

15.3 FL OZ (460 mL) as dispensed